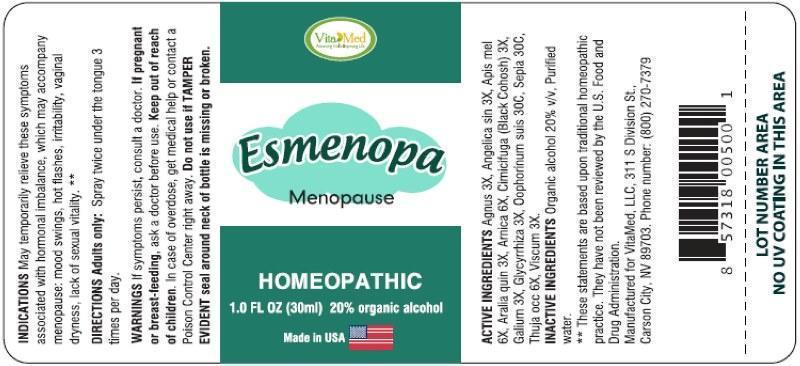 DRUG LABEL: Esmenopa
NDC: 64249-0003 | Form: SPRAY
Manufacturer: VitaMed, LLC
Category: homeopathic | Type: HUMAN PRESCRIPTION DRUG LABEL
Date: 20140818

ACTIVE INGREDIENTS: CHASTE TREE 3 [hp_X]/1 mL; ANGELICA SINENSIS ROOT 3 [hp_X]/1 mL; APIS MELLIFERA 6 [hp_X]/1 mL; AMERICAN GINSENG 3 [hp_X]/1 mL; ARNICA MONTANA 6 [hp_X]/1 mL; BLACK COHOSH 3 [hp_X]/1 mL; GALIUM APARINE 3 [hp_X]/1 mL; GLYCYRRHIZA GLABRA 3 [hp_X]/1 mL; SUS SCROFA OVARY 30 [hp_C]/1 mL; SEPIA OFFICINALIS JUICE 30 [hp_C]/1 mL; THUJA OCCIDENTALIS LEAFY TWIG 6 [hp_X]/1 mL; VISCUM ALBUM FRUITING TOP 3 [hp_X]/1 mL
INACTIVE INGREDIENTS: WATER; ALCOHOL

DRUG FACTS

ACTIVE INGREDIENTS:

Agnus Castus 3X, Angelica Sinensis Radix 3X, Apis Mellifica 6X, Aralia Quinquefolia 3X, Arnica Montana 6X, Cimicifuga Racemosa 3X, Galium Aparine 3X, Glycyrrhiza Glabra 3X, Oophorinum Suis 300C, Sepia 30C, Thuja Occidentalis 6X, Viscum ALbum 3X

INDICATIONS:

May temporarily relieve these symptoms associated with hormonal imbalance, which may accompany menopause: mood swings, hot flashes, irritability, vaginal dryness, lack of sexual vitality. **

**These statements are based upon traditional homeopathic practice. They have not been reviewed by the U.S. Food and Drug Administration.

WARNINGS:

If symptoms persist, consult a doctor.

If pregnant or breast-feeding, ask a doctor before use.

Keep out of reach of children. In case of overdose, get medical help or contact a Poison Control Center right away.

Do not use if TAMPER EVIDENT seal around neck of bottle is missing or broken.

Keep out of reach of children. In case of overdose, get medical help or contact a Poison Control Center right away.

DIRECTIONS:

Adults only: Spray twice under the tongue 3 times per day.

INDICATIONS:

May temporarily relieve these symptoms associated with hormonal imbalance, which may accompany menopause: mood swings, hot flashes, irritability, vaginal dryness, lack of sexual vitality. **

**These statements are based upon traditional homeopathic practice. They have not been reviewed by the U.S. Food and Drug Administration.

INACTIVE INGREDIENTS:

Organic alcohol 20% v/v, Purified water.

QUESTIONS:

Manufactured for VitaMed, LLC, 311 S Division St.,

Carson City, NV 89703. Phone number: (800) 270-7379

PACKAGE LABEL DISPALY

Vita Med

Esmenopa

Menopause

HOMEOPATHIC

1 FL OZ (30 ml)